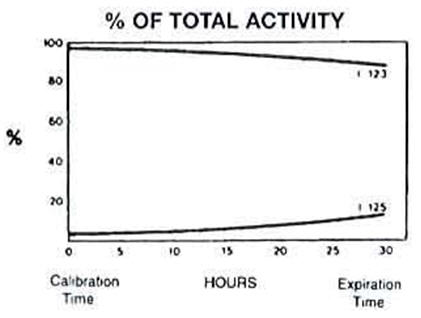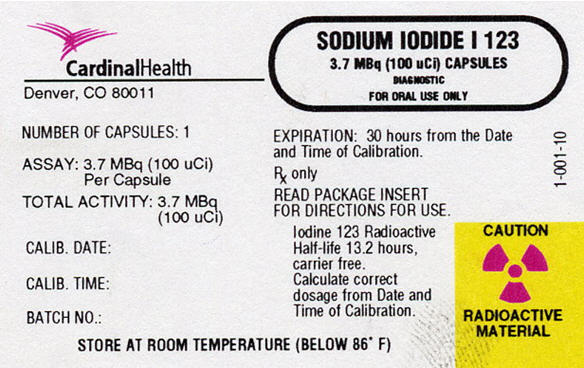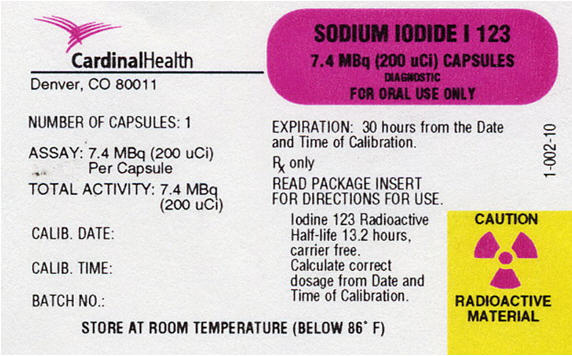 DRUG LABEL: Sodium Iodide I 123
NDC: 48815-1001 | Form: CAPSULE, GELATIN COATED
Manufacturer: Cardinal Health 418, Inc
Category: prescription | Type: HUMAN PRESCRIPTION DRUG LABEL
Date: 20180417

ACTIVE INGREDIENTS: SODIUM IODIDE I-123 100 uCi/1 1
INACTIVE INGREDIENTS: SUCROSE; SODIUM THIOSULFATE

Sodium Iodide I 123
Diagnostic-Capsules
for Oral Administration

DESCRIPTION

Sodium Iodide I 123 (Na^123I) for diagnostic use is supplied in capsules for oral administration. The capsules are available in strengths of 3.7 and 7.4 megabecquerels (MBq) (100 and 200 μCi) I 123 at time of calibration. Each capsule contains 0.3 µg - 3 µg Sodium Thiosulfate as a stabilizer.

The radionuclidic composition at calibration is not less than 97.0 percent I 123, not more than 2.9 percent I 125 and not more than 0.1 percent all others (I 121 or Te 121.) The radionuclidic composition at expiration time is not less than 87.2 percent I 123, not more than 12.4 percent I 125 and not more than 0.4 percent all others. The ratio of the concentration of I 123 and I 125 changes with time. Graph 1 shows the maximum concentration of each as a function of time.

Graph 1 Radionuclidic Concentration of I 123 and I 125

Physical Characteristics

Sodium Iodide I 123 decays by electron capture with a physical half-life of 13.2 hours. The photon that is useful for detection and imaging studies is listed in Table 1.

Table 1 Principal Radiation Emission Data^1
Radiation | Mean %/Disintegration | Mean Energy (keV)
Gamma-2 | 83.4 | 159
^1 Kocher, David C., Radioactive Decay Data Tables, DOE/TIC-11026, 122, (1981)

External Radiation

The specific gamma ray constant for I 123 is 1.6 R/hr-mCi at 1 cm. The first half value thickness of lead (Pb) for I 123 is 0.005 cm. A range of values for the relative attenuation of the radiation emitted by this radionuclide that results from the interposition of various thicknesses of Pb is shown in Table 2. For example, the use of 1.63 cm of lead will decrease the external radiation exposure by a factor of about 1,000.

Table 2 Radiation Attenuation by Lead Shielding^2
Shield Thickness (Pb), cm | Coefficient of Attenuation
0.036 | 0.5
0.120 | 10^-1
0.240 | 10^-2
0.358 | 10^-3
0.477 | 10^-4
^2 Shleien, Bernard, The Health Physics and Radiological Health Handbook, Table 6.1.2, 169, (1992)

Note that these estimates of attenuation do not take into consideration the presence of contaminants.

To correct for physical decay of I 123, the fractions that remain at selected intervals after the time of calibration are shown in Table 3.

Table 3 Sodium Iodide I 123 Decay Chart: Half-Life 13.2 Hours
Hours | Fraction Remaining | Hours | Fraction Remaining
0* | 1.000 | 18 | .389
3 | .854 | 21 | .332
6 | .730 | 24 | .284
9 | .623 | 27 | .242
12 | .535 | 30 | .207
15 | .455
*Time of Calibration

CLINICAL PHARMACOLOGY

Sodium Iodide I 123 is readily absorbed from the upper gastrointestinal tract. Following absorption, the iodide is distributed primarily within the extracellular fluid of the body. It is trapped and organically bound by the thyroid and concentrated by the stomach, choroid plexus and salivary glands. It is excreted by the kidneys.

The fraction of the administered dose which is accumulated in the thyroid gland may be a measure of thyroid function in the absence of unusually high or low iodine intake or administration of certain drugs which influence iodine accumulation by the thyroid gland. Accordingly, the patient should be questioned carefully regarding previous medication and/or procedures involving radiographic media. Normal subjects can accumulate approximately 10-50% of the administered iodine dose in the thyroid gland, however, the normal and abnormal ranges are established by individual physician's criteria. The mapping (imaging) of Sodium Iodide I 123 distribution in the thyroid gland may provide useful information concerning thyroid anatomy and definition of normal and/or abnormal functioning of tissue within the gland.

INDICATION AND USE

Administration of Sodium Iodide I 123 is indicated as a diagnostic procedure to be used in evaluating thyroid function and/or morphology.

CONTRAINDICATIONS

To date there are no known contraindications to the use of Sodium Iodide I 123 capsules.

WARNINGS

Females of childbearing age and children under 18 should not be studied unless the benefits anticipated from the performance of the test outweigh the possible risk of exposure to the amount of ionizing radiation associated with the test.

PRECAUTIONS

General

The contents of the capsule are radioactive. Adequate shielding of the preparation must be maintained at all times.

Do not use after the expiration time and date (30 hours after calibration time) stated on the label.

The prescribed Sodium Iodide I 123 dose should be administered as soon as practical from the time of receipt of product (i.e., as close to calibration time as possible) in order to minimize the fraction of radiation exposure due to relative increase of radionuclidic contaminants with time.

Sodium Iodide I 123, as well as other radioactive drugs, must be handled with care and appropriate safety measures should be used to minimize radiation exposure to clinical personnel. Care should also be taken to minimize radiation exposure to the patient consistent with proper patient management.

Radiopharmaceuticals should be used only by physicians who are qualified by training and experience in the safe use and handling of radionuclides and whose experience and training have been approved by the appropriate government agency authorized to license the use of radionuclides.

Carcinogenesis, Mutagenesis, Impairment of Fertility

No long-term animal studies have been performed to evaluate carcinogenic potential, mutagenic potential, or whether Sodium Iodide I 123 affects fertility in males or females.

Pregnancy

Animal reproduction studies have not been conducted with this drug. It is also not known whether Sodium Iodide I 123 can cause fetal harm when administered to a pregnant woman or can affect reproductive capacity. Sodium Iodide I 123 should be given to a pregnant woman only if clearly needed.

Ideally examinations using radiopharmaceuticals, especially those elective in nature, in women of childbearing capability should be performed during the first few (approximately ten) days following the onset of menses.

Nursing Mothers

Since I 123 is excreted in human milk, formula-feeding should be substituted for breast-feeding if the agent must be administered to the mother during lactation.

Pediatric Use

Safety and effectiveness in children have not been established.

ADVERSE REACTIONS

Although rare, reactions associated with the administration of Sodium Iodide isotopes for diagnostic use include, in decreasing order of frequency, nausea, vomiting, chest pain, tachycardia, itching skin, rash and hives.

DOSAGE AND ADMINISTRATION

The recommended oral dose for the average patient (70 kg) is 3.7 to 14.8 MBq (100-400 µCi). The lower part of the dosage range 3.7 MBq (100 µCi) is recommended for uptake studies alone, and the higher part 14.8 MBq (400 µCi) for thyroid imaging. The determination of I 123 concentration in the thyroid gland may be initiated at six hours after administering the dose and should be measured in accordance with standardized procedures.

The patient dose should be measured by a suitable radioactive calibration system immediately prior to administration. The capsules can be utilized up to thirty (30) hours after calibration time and date. Thereafter, discard the capsules in accordance with standard safety procedures. The user should wear waterproof gloves at all times when handling the capsules or container.

Radiation Dosimetry

The estimated absorbed radiation doses to several organs of an average patient (70 kg) from oral administration of the maximum dose of 14.8 MBq (400 µCi) of I 123 are shown in Table 4 for thyroid uptakes of 5, 15, and 25%. For comparison at these three values of thyroid uptake, the estimated radiation doses from doses of 3.7 MBq (100 µCi) I 131, also used as thyroid imaging agent, are also included.

Table 4 Radiation Dose Estimates as a Function of Maximum Thyroid Uptake for I 123* Sodium Iodide At Time of Calibration and Expiry Compared to I 131
Target Organ | Maximum Thyroid Uptake (%) | Estimated Radiation Absorbed Doses
Target Organ | Maximum Thyroid Uptake (%) | I 123 mGy/14.8 MBq (rads/400 µCi) |  |  |  | I 131 mGy/3.7 MBq (rads/100 µCi)
Target Organ | Maximum Thyroid Uptake (%) | TOC |  | TOE
Thyroid | 5 | 25 | (2.5) | 75 | (7.5) | 260 | (26)
 | 15 | 77 | (7.7) | 230 | (23) | 780 | (78)
 | 25 | 130 | (13) | 410 | (41) | 1300 | (130)
Liver | 5 | 0.089 | (0.0089) | 0.13 | (0.013) | 0.16 | (0.016)
 | 15 | 0.10 | (0.010) | 0.18 | (0.018) | 0.28 | (0.028)
 | 25 | 0.11 | (0.011) | 0.24 | (0.024) | 0.41 | (0.041)
Ovaries | 5 | 0.18 | (0.018) | 0.19 | (0.019) | 0.18 | (0.018)
 | 15 | 0.17 | (0.017) | 0.18 | (0.018) | 0.18 | (0.018)
 | 25 | 0.16 | (0.016) | 0.18 | (0.018) | 0.17 | (0.017)
Red Marrow | 5 | 0.12 | (0.012) | 0.16 | (0.016) | 0.15 | (0.015)
 | 15 | 0.12 | (0.012) | 0.18 | (0.018) | 0.21 | (0.021)
 | 25 | 0.13 | (0.013) | 0.19 | (0.019) | 0.27 | (0.027)
Stomach Wall | 5 | 0.96 | (0.096) | 0.98 | (0.098) | 1.7 | (0.17)
 | 15 | 0.89 | (0.089) | 0.91 | (0.091) | 1.5 | (0.15)
 | 25 | 0.82 | (0.082) | 0.85 | (0.085) | 1.4 | (0.14)
Small Intestine | 5 | 0.70 | (0.070) | 0.71 | (0.071) | 1.2 | (0.12)
 | 15 | 0.65 | (0.065) | 0.67 | (0.067) | 1.1 | (0.11)
 | 25 | 0.60 | (0.060) | 0.62 | (0.062) | 0.99 | (0.099)
Testes | 5 | 0.076 | (0.0076) | 0.089 | (0.0089) | 0.12 | (0.012)
 | 15 | 0.072 | (0.0072) | 0.087 | (0.0087) | 0.12 | (0.012)
 | 25 | 0.068 | (0.0068) | 0.085 | (0.0085) | 0.12 | (0.012)
Bladder | 5 | 1.7 | (0.17) | 1.7 | (0.17) | 2.9 | (0.29)
 | 15 | 1.6 | (0.16) | 1.6 | (0.16) | 2.7 | (0.27)
 | 25 | 1.4 | (0.14) | 1.5 | (0.15) | 2.4 | (0.24)
Skeleton | 5 | 0.11 | (0.011) | 0.16 | (0.016) | 0.12 | (0.012)
 | 15 | 0.12 | (0.012) | 0.18 | (0.018) | 0.18 | (0.018)
 | 25 | 0.14 | (0.014) | 0.21 | (0.021) | 0.24 | (0.024)
Total Body | 5 | 0.11 | (0.011) | 0.16 | (0.016) | 0.24 | (0.024)
 | 15 | 0.14 | (0.014) | 0.25 | (0.025) | 0.47 | (0.047)
 | 25 | 0.17 | (0.017) | 0.35 | (0.035) | 0.70 | (0.070)
*Concentration at Time of Calibration: 97% I 123, 2.9% I 125, 0.1% Te 121
Concentration at Time of Expiry: 87.2% I 123, 12.4% I 125, 0.4% Te 121
All Iodine Kinetics treated as in MIRD Dose Estimate Report 5. Bladder voiding interval, 4.8 hours.
Tellurium 121 dosimetry taken from ICRP 30.

HOW SUPPLIED

Sodium Iodide I 123 is supplied as capsules for oral administration in strengths of 3.7 MBq (100 µCi) and 7.4 MBq (200 µCi) at time of calibration. Each gelatin capsule contains 0.45 - 0.65 g of sucrose. The capsules are packaged in plastic vials containing either one or five capsules of a single strength per vial. The plastic vial is packaged in a lead shield with a label identical to that affixed to the plastic vial. A package insert is supplied with each lead shield.

The -I (Iodine) content for a 100 µCi capsule is 5.2 ng and the -I content for a 200 µCi capsule is 10.4 ng at TOC.

Dispense and preserve capsules in well-closed containers that are adequately shielded. Store at room temperature, below 86°F.

The contents of the capsules are radioactive. Adequate shielding and handling precautions must be maintained.

THIS PACKAGE INSERT ISSUED APRIL 2018

CardinalHealth
Denver, CO 80011 (303) 343-6800

Sodium Iodide I 123
1-020-16

PRINCIPAL DISPLAY PANEL - 100 µCi CAPSULE

100 µCi Capsule

CardinalHealth
Denver, CO 80011

NUMBER OF CAPSULES: 1

ASSAY: 3.7 MBq (100 uCi) Per Capsule

TOTAL ACTIVITY: 3.7 MBq (100 uCi)

CALIB. DATE:

CALIB. TIME:

BATCH NO.:

SODIUM IODIDE I 123
3.7 MBq (100 uCi) CAPSULES
DIAGNOSTIC
FOR ORAL USE ONLY

EXPIRATION: 30 hours from the Date
and Time of Calibration.

Rx only

READ PACKAGE INSERT
FOR DIRECTIONS FOR USE.

Iodine 123 Radioactive
Half-life 13.2 hours,
carrier free.
Calculate correct
dosage from Date and
Time of Calibration

STORE AT ROOM TEMPERATURE (BELOW 86° F)

CAUTION RADIOACTIVE MATERIAL

1-001-10

PRINCIPAL DISPLAY PANEL - 200 µCi CAPSULE

200 µCi Capsule

CardinalHealth
Denver, CO 80011

NUMBER OF CAPSULES: 1

ASSAY: 7.4 MBq (200 uCi) Per Capsule

TOTAL ACTIVITY: 7.4 MBq (200 uCi)

CALIB. DATE:

CALIB. TIME:

BATCH NO.:

SODIUM IODIDE I 123
7.4 MBq (200 uCi) CAPSULES
DIAGNOSTIC
FOR ORAL USE ONLY

EXPIRATION: 30 hours from the Date
and Time of Calibration.

Rx only

READ PACKAGE INSERT
FOR DIRECTIONS FOR USE.

Iodine 123 Radioactive
Half-life 13.2 hours,
carrier free.
Calculate correct
dosage from Date and
Time of Calibration

STORE AT ROOM TEMPERATURE (BELOW 86° F)

CAUTION RADIOACTIVE MATERIAL

1-002-10